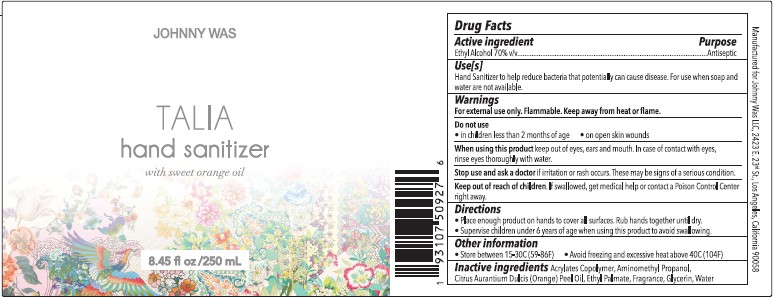 DRUG LABEL: Hand Sanitizer
NDC: 80981-110 | Form: LIQUID
Manufacturer: Johnny Was
Category: otc | Type: HUMAN OTC DRUG LABEL
Date: 20201201

ACTIVE INGREDIENTS: ALCOHOL 70 mL/100 mL
INACTIVE INGREDIENTS: WATER; ETHYL PALMATE; BUTYL ACRYLATE/METHYL METHACRYLATE/METHACRYLIC ACID COPOLYMER (18000 MW); AMINOMETHYLPROPANOL; GLYCERIN

Hand Sanitizer

Active Ingredient

Ethyl Alcohol 70% v/v

Purpose

Antiseptic

Use(s)

Hand Sanitizer to help reduce bacteria that potentially cause disease. For use when soap and water are not available.

Warnings

For external use only. Flammable. Keep away from heat or flame.

Do not use

in children under 2 months of age

on open wounds

When using this product

keep out of eyes, ears and mouth. In case of contact with eyes, rinse eyes thoroughly with water.

Stop use and ask a doctor

if irritation occurs. These may be signs of a serious condition.

Keep out of reach of children.

if swallowed, get medical help or contact a Poison Control Center right away.

Directions

Place enough product on hands to cover all surfaces. Rub together until dry.

Supervise children under 6 years of age when using this product to avoid swallowing.

Other Information

Store between 15-30C (59-86F)

Avoid Freezing and excessive heat above 40C (104F)

Inactive Ingredients

Acrylates Copolymer, Aminomethyl Propanol, Citrus Aurantium Dulcis (Orange) Peel Oil, Ethyl Palmate, Fragrance, Glycerin, Water